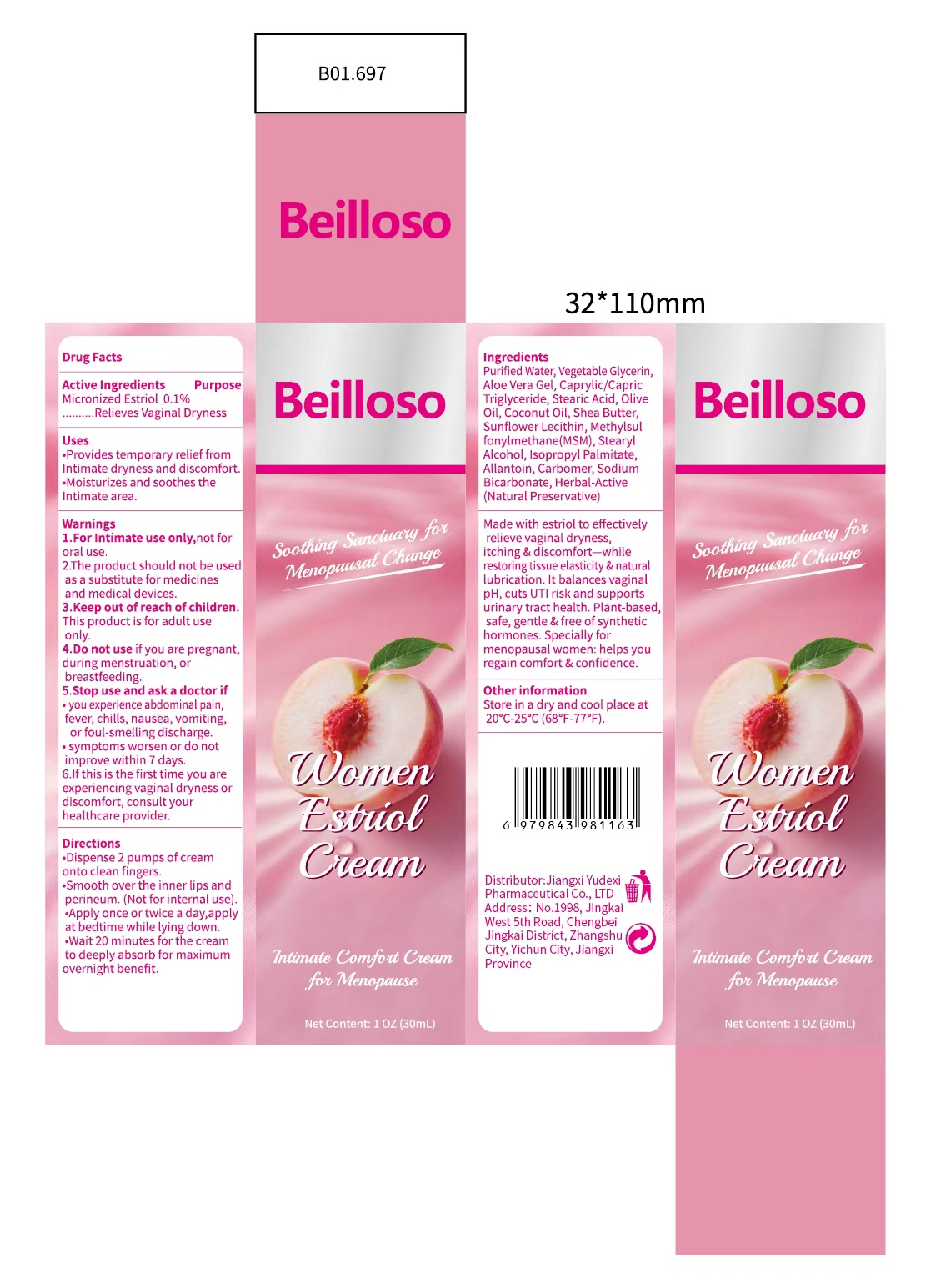 DRUG LABEL: Beilloso Women  Estriol
NDC: 85248-137 | Form: CREAM
Manufacturer: Jiangxi Yudexi Pharmaceutical Co., LTD
Category: otc | Type: HUMAN OTC DRUG LABEL
Date: 20260209

ACTIVE INGREDIENTS: ESTRIOL 0.1 g/100 mL
INACTIVE INGREDIENTS: CAPRYLIC/CAPRIC TRIGLYCERIDE; DIMETHYL SULFONE; STEARIC ACID; SHEA BUTTER; SODIUM BICARBONATE; STEARYL ALCOHOL; WATER; ALOE VERA LEAF; CARBOMER; ALLANTOIN; OLIVE OIL; ISOPROPYL PALMITATE; GLYCERIN

85248-137

Active Ingredient

Micronized Estriol 0.1%

Purpose

Relieves Vaginal Dryness

Use

.Provides temporary relief from Intimate dryness and discomfort.Moisturizes and soothes theIntimate area.

Warnings

1.For lntimate use only,not for oral use.
2.The product should not be use(as a substitute for medicinesad medical devices.

Do not use if you are pregnant,during menstruation, or breastfeeding.

When Using

lf this is the first time you are experiencing vaginal dryness or discomfort. consult your healthcare provider.

Stop Use

·you experience abdominal pain.fever, chills,nausea.vomiting of foul-smelling discharge.·symptoms worsen or do not
improve within 7 days.

Ask Doctor

·you experience abdominal pain.fever, chills,nausea.vomiting of foul-smelling discharge.·symptoms worsen or do not
improve within 7 days.

Keep Oot Of Reach Of Children

.Keep out of reach of children,This product is for adult use onlv.

Directions

.Dispense 2 pumps ofcream onto clean fingers. ·Smooth over the inner lips and perineum.(Not for internal use). ·Apply once or twice a day.apply once or twice a day,apply at bedtime while lying down. ·Wait 20 minutes for the cream to deeply absorb for maximum overnight benefit.

Other information

Store in a dry and cool place at 20°-25°C(68°F-77°F).

Inactive ingredients

Purified Water, Vegetable Glycerin, Aloe Vera Gel.Caprylic/Capric Triglyceride.Scleroc Acid， olive Oil.Coconut Oil.Shea Butter. Methylsulfonylmethane(MsM).Stearyl Alcohol,Isopyl Palmitate,Allantoin.Carbomer, Sodium Bicarbonate.Herbal Extract(Natural Preservative)